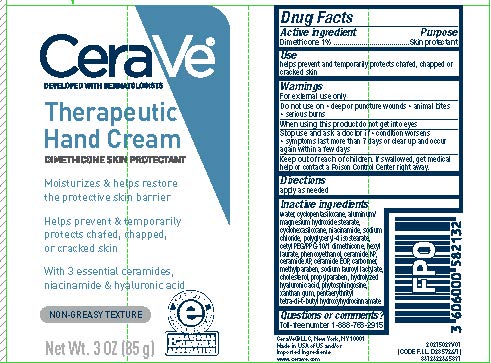 DRUG LABEL: CeraVe Developed with Dermatologists Therapeutic Hand
NDC: 49967-925 | Form: CREAM
Manufacturer: L'Oreal USA Products Inc
Category: otc | Type: HUMAN OTC DRUG LABEL
Date: 20231228

ACTIVE INGREDIENTS: DIMETHICONE 10 mg/1 g
INACTIVE INGREDIENTS: WATER; CYCLOMETHICONE 5; CYCLOMETHICONE 6; NIACINAMIDE; SODIUM CHLORIDE; POLYGLYCERYL-4 ISOSTEARATE; HEXYL LAURATE; PHENOXYETHANOL; CERAMIDE 3; CERAMIDE 6 II; CERAMIDE 1; CARBOMER HOMOPOLYMER, UNSPECIFIED TYPE; METHYLPARABEN; SODIUM LAUROYL LACTYLATE; CHOLESTEROL; PROPYLPARABEN; PHYTOSPHINGOSINE; HYALURONIC ACID; XANTHAN GUM; PENTAERYTHRITOL TETRAKIS(3-(3,5-DI-TERT-BUTYL-4-HYDROXYPHENYL)PROPIONATE)

Drug Facts

Active ingredient

Dimethicone 1%

Purpose

Skin protectant

Use

helps prevent and temporarily protects chafed, chapped or cracked skin

Warnings

For external use only

Do not use on

- deep or puncture wounds
- animal bites
- serious burns

When using this product

do not get into eyes

Stop use and ask a doctor if

- condition worsens
- symptoms last more than 7 days or clear up and occur again within a few days

Keep out of reach of children.

If swallowed, get medical help or contact a Poison Control Center right away.

Directions

apply as needed

Inactive Ingredients

water, cyclopentasiloxane, aluminum/magnesium hydroxide stearate, cyclohexasiloxane, niacinamide, sodium chloride, polyglyceryl-4 isostearate, cetyl PEG/PPG-10/1 dimethicone, hexyl laurate, phenoxyethanol, ceramide NP, ceramide AP, ceramide EOP, carbomer, methylparaben, sodium lauroyl lactylate, cholesterol,. Propylparaben, hydrolyzed hyaluronic acid, phytosphingosine, xanthan gum, pentaerythrityl tetra-di-t-butyl hydroxyhydrocinnamate

Questions or comments?

Toll-free number 1-888-768-2915

www.cerave.com